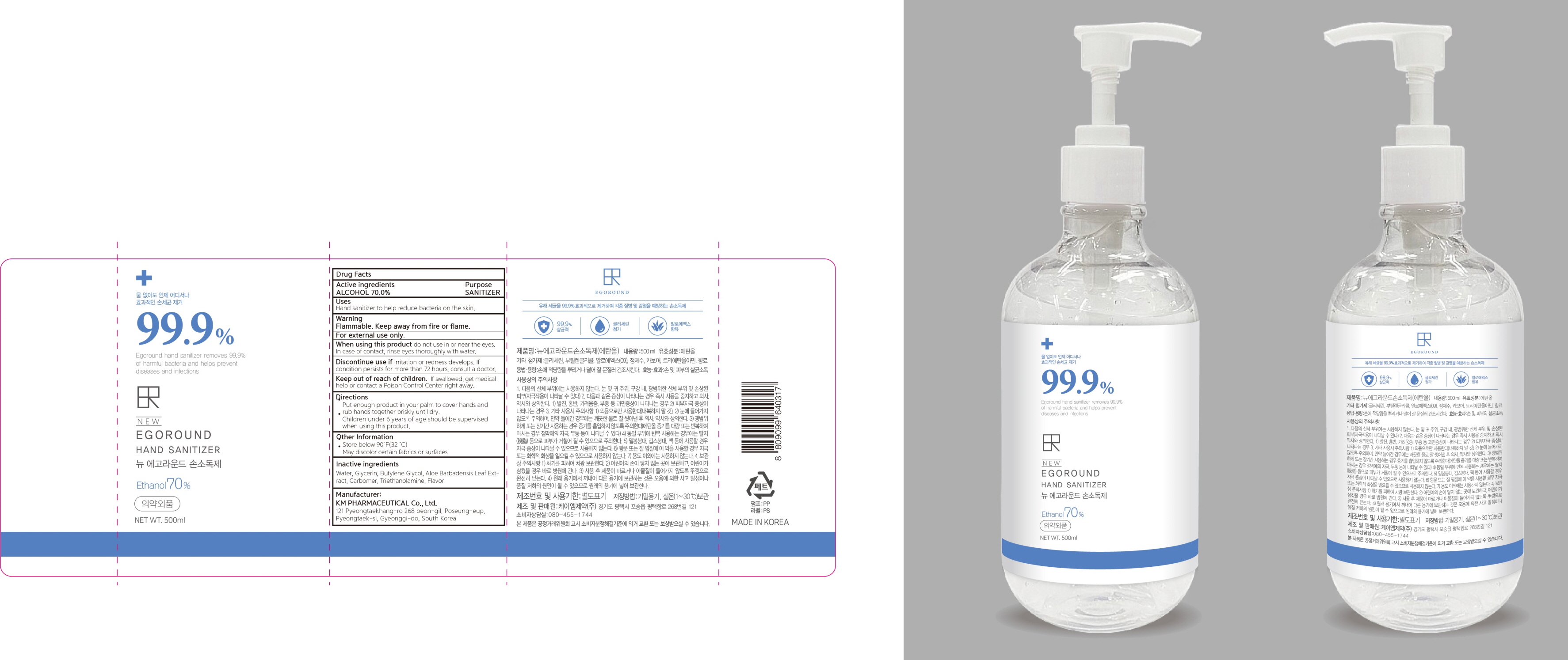 DRUG LABEL: NEW EGOROUND HAND SANITIZER
NDC: 50555-070 | Form: GEL
Manufacturer: KMPHARMACEUTICAL Co.,Ltd.
Category: otc | Type: HUMAN OTC DRUG LABEL
Date: 20200420

ACTIVE INGREDIENTS: ALCOHOL 350 mL/500 mL
INACTIVE INGREDIENTS: Water; Glycerin; Butylene Glycol; ALOE VERA LEAF; CARBOMER HOMOPOLYMER, UNSPECIFIED TYPE; TROLAMINE

ACTIVE INGREDIENT

Active ingredients: ALCOHOL 70.0%

INACTIVE INGREDIENT

Inactive Ingredients:

Water, Glycerin, Butylene Glycol, Aloe Barbadensis Leaf Extract, Carbomer, Triethanolamine, Flavor

PURPOSE

Purpose: SANITIZER

WARNINGS

Flammable. Keep away from fire or flame.
For external use only.

When using this product
do not use in or near the eyes.
In case of contact, rinse eyes thoroughly with water.

Discontinue use if
irritation or redness develops. If condition persists for more than 72 hours, consult a doctor.

KEEP OUT OF REACH OF CHILDREN

If swallowed, get medical help or contact a Poison Control Center right away.

Uses

Hand sanitizer to help reduce bacteria on the skin.

Directions

Put enough product in your palm to cover hands and rub hands together briskly until dry.
Children under 6 years of age should be supervised when using this product.

Other Information

Store below 90°F(32°C)
May discolor certain fabrics or surfaces